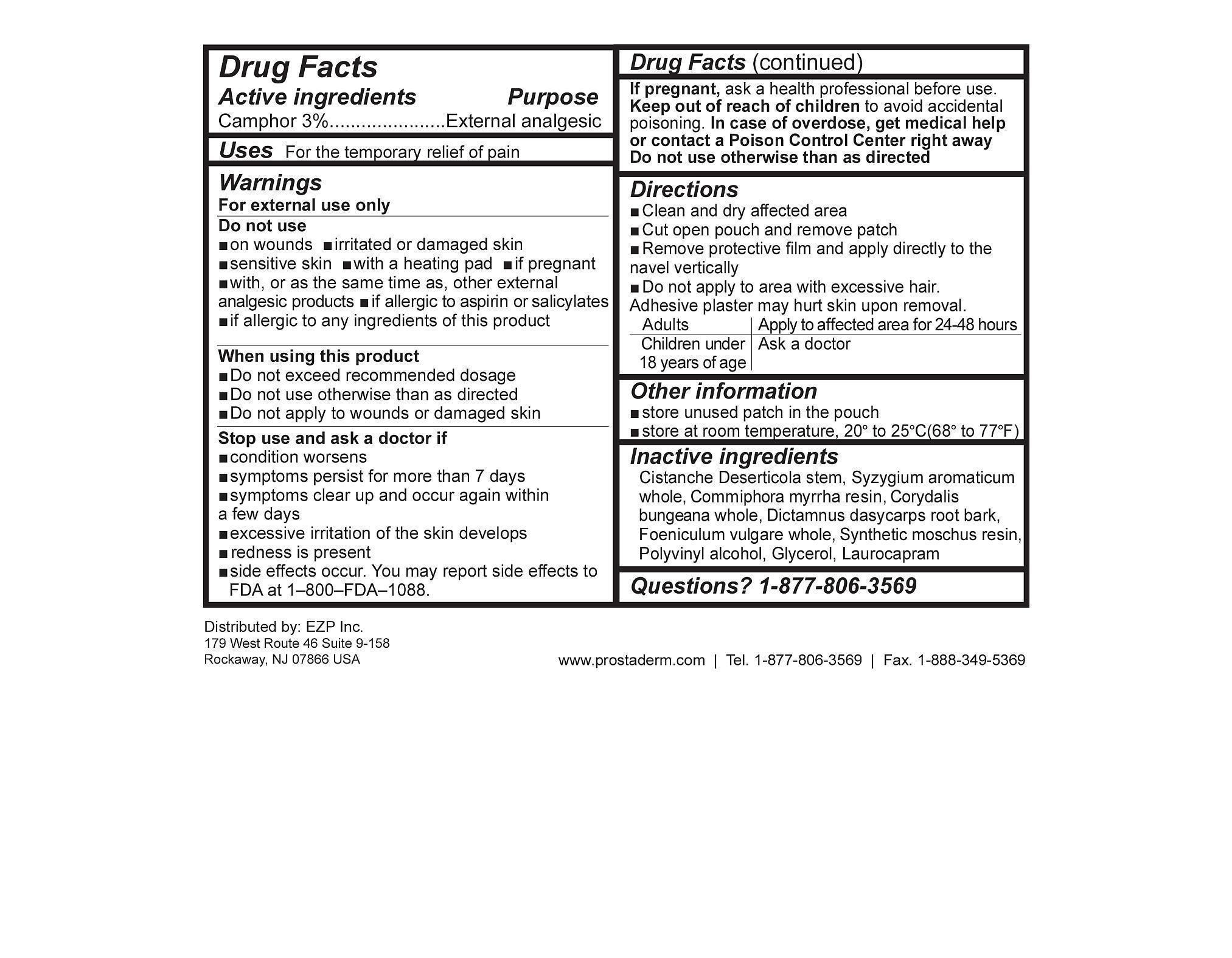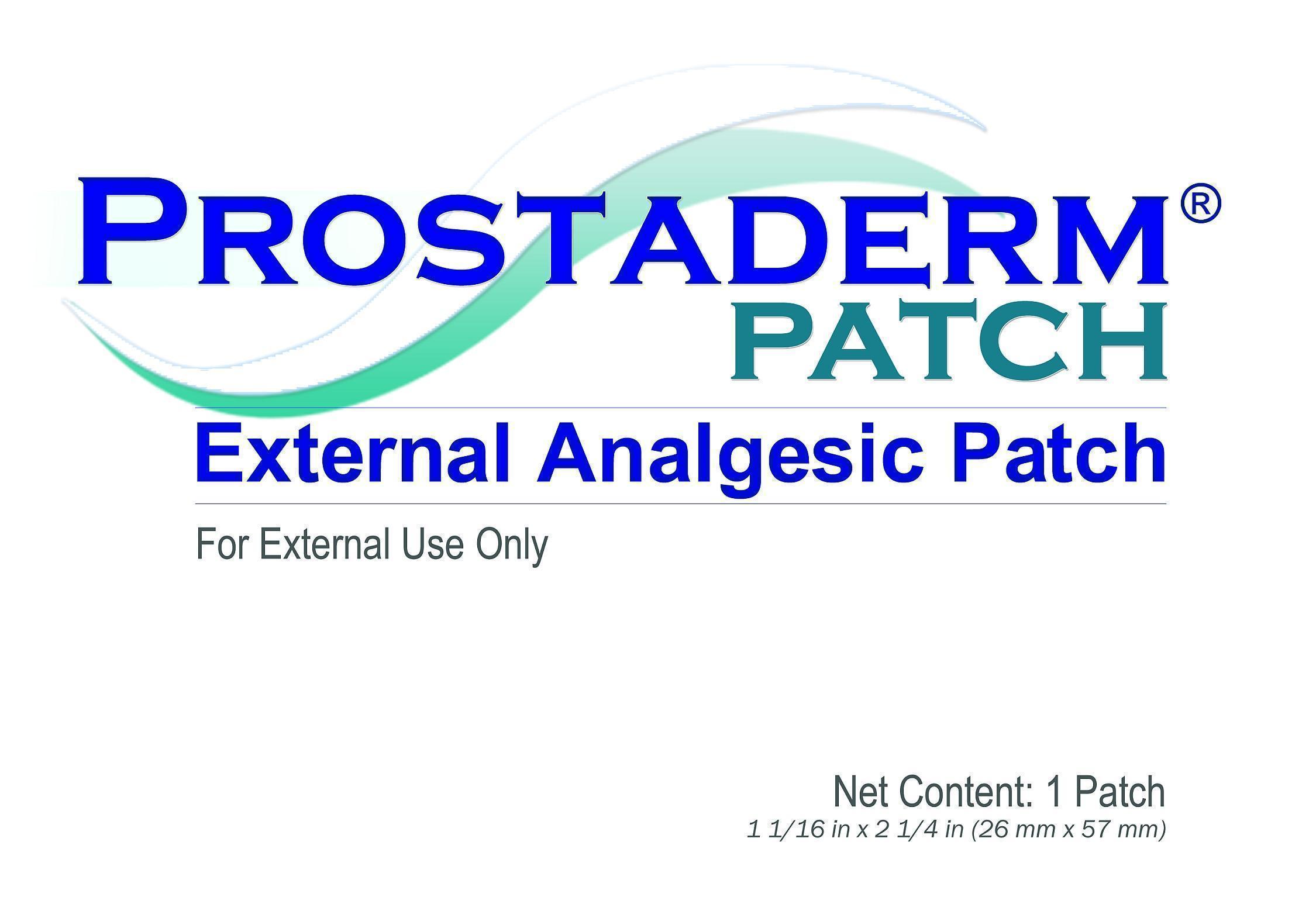 DRUG LABEL: Prostaderm
NDC: 69446-100 | Form: PLASTER
Manufacturer: EZP Corporation
Category: otc | Type: HUMAN OTC DRUG LABEL
Date: 20150224

ACTIVE INGREDIENTS: CAMPHOR (SYNTHETIC) 3 1/100 1
INACTIVE INGREDIENTS: CISTANCHE DESERTICOLA STEM; SYZYGIUM AROMATICUM WHOLE; COMMIPHORA MYRRHA WHOLE; CORYDALIS BUNGEANA WHOLE; DICTAMNUS DASYCARPUS ROOT BARK; FOENICULUM VULGARE WHOLE; MOSCHUS MOSCHIFERUS MUSK SAC RESIN; POLYVINYL ALCOHOL; GLYCEROL FORMAL; LAUROCAPRAM

Prostaderm

Active ingredients Purpose

Camphor 3%...........................External analgesic

PURPOSE

Uses For the temporary relief of pain

When using this product

- Do not exceed recommended dosage
- Do not use otherwise than as directed
- Do not apply to wounds or damaged skin

Stop use and ask a doctor if

- condition worsens
- symptoms persist for more than 7 days
- symptoms clear up and occur again within a few days
- excessive irritation of the skin develops
- redness is present
- side effects occur. You may report side effects to FDA at
  1–800–FDA–1088.

PREGNANCY OR BREAST FEEDING

If pregnant or breast-feeding, ask a health professional before use.

KEEP OUT OF REACH OF CHILDREN

Keep this and all drugs out of reach of children.

In case of overdose, get medical help or contact a Poison Control Center right away
Do not use otherwise than as directed

- Questions?1-877-806-3569

Directions

- Clean and dry affected area
- Cut open pouch and remove patch
- Remove Protective film and apply directly to the navel vertically
- Do not apply to area with excessive hair. Highly adhesive patch, may hurt skin upon removal

Adults | Apply to affected area for 24-48 hours
Children under 18 years of age | Ask a doctor

WARNINGS

For external use only.

Do not use otherwise than as directed

INDICATIONS AND USAGE

Uses For the temporary relief of pain.

INACTIVE INGREDIENT

Cistanche Deserticola stem, Syzygium aromaticum whole, Commiphora myrrha resin, Corydalis bungeana whole, Dictamnus dasycarps root bark, Foeniculum vulgare whole, Synthetic moschus resin, Polyvinyl alcohol, Glycerol, Laurocapram